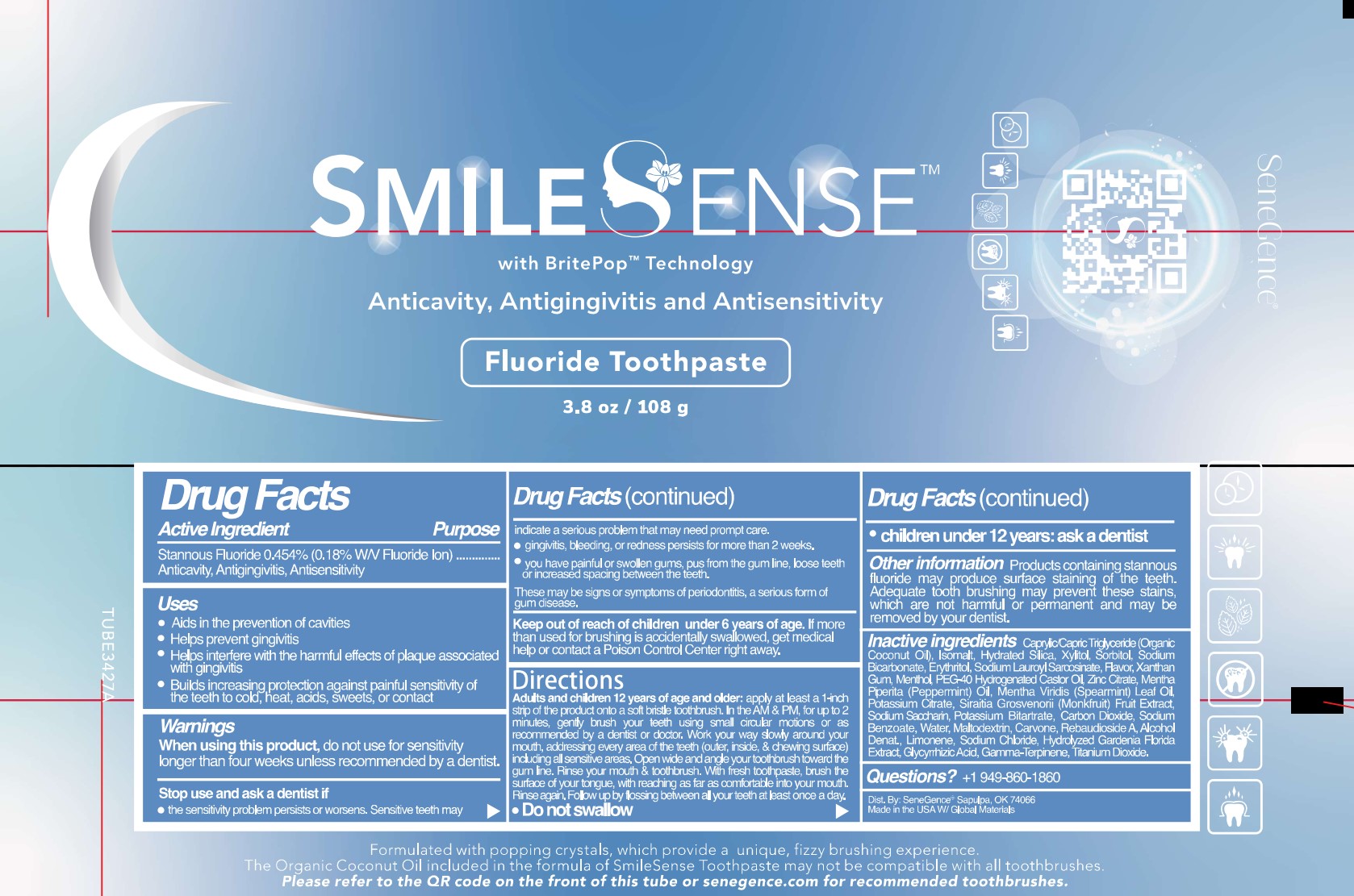 DRUG LABEL: SmileSense
NDC: 72644-639 | Form: PASTE, DENTIFRICE
Manufacturer: SGII, INC
Category: otc | Type: HUMAN OTC DRUG LABEL
Date: 20240701

ACTIVE INGREDIENTS: STANNOUS FLUORIDE 0.11 g/100 g
INACTIVE INGREDIENTS: GARDENIA JASMINOIDES WHOLE; GLYCYRRHIZIN; XANTHAN GUM; CARBON DIOXIDE; MEDIUM-CHAIN TRIGLYCERIDES; CARVONE, (+)-; POTASSIUM CITRATE; POLYOXYL 40 HYDROGENATED CASTOR OIL; ZINC CITRATE; SIRAITIA GROSVENORII FRUIT; SORBITOL; SODIUM BICARBONATE; ERYTHRITOL; MENTHOL; PEPPERMINT OIL; SODIUM BENZOATE; WATER; SODIUM CHLORIDE; .GAMMA.-TERPINENE; ISOMALT; HYDRATED SILICA; XYLITOL; MALTODEXTRIN; REBAUDIOSIDE A; LIMONENE, (+)-; SODIUM LAUROYL SARCOSINATE; SPEARMINT OIL; SACCHARIN SODIUM; POTASSIUM BITARTRATE; ALCOHOL; TITANIUM DIOXIDE

SmileSense Fluoride Toothpaste

Active ingredient

Stannous Fluoride 0.454% (0.18% W/V Fluoride Ion)

Purpose

Stannous Fluoride 0.454% (0.18% W/V Fluoride Ion).................Anticavity, Antigingivitis, Antisensitivity

Uses

- Aids in the prevention of cavities
- Helps prevent gingivitis
- Helps interfere with the harmful effects of plaque associated with gingivitis
- Builds increasing protection against painful sensitivity of the teeth to cold, heat, acids, sweets, or contact

Warnings

When using this product, do not use for sensitivity longer than four weeks unless recommended by a dentist.

Stop use and ask a dentist if

- the sensitivity problem persists or worsens. Sensitive teeth may indicate a serious problem that may need prompt care.
- gingivitis, bleeding, or redness persists for more than 2 weeks.
- you have painful or swollen gums, pus from the gum line, loose teeth, or increased spacing between the teeth.

These may be signs or symptoms of periodontitis, a serious form of gum disease.

Keep out of reach of children, under 6 years of age. If more than used for brushing is accidentally swallowed, get medical help or contact a Poison Control Center right away.

Directions

Adults and children 12 years of age and older: apply at least a 1-inch strip of the product onto a soft bristle toothbrush. In the AM & PM, for up to 2 minutes, gently brush your teeth using small, circular motions or as recommended by a dentist or doctor. Work your way slowly around your mouth, addressing every area of the teeth (outer, inside & chewing surface) including all sensitive areas. Open wide and angle your toothbrush toward the gum line. Rinse your mouth & toothbrush. With fresh toothpaste, brush the surface of your tongue, with reaching as far as comfortable into your mouth. Rinse again. Follow-up by flossing between all your teeth at least once a day.

- Do not swallow
- children under 12 yeasr: ask a dentist

Other information

Products containing stannous fluoride may produce surface staining of the teeth. Adequate tooth brushing may prevent these stains, which are not harmful or permanent and may be removed by your dentist.

Inactive ingredients

Caprylic/Capric Triglyceride (Organic Coconut Oil), Isomalt, Hydrated Silica, Xylitol, Sorbitol, Sodium Bicarbonate, Erythritol, Sodium Lauroyl Sarcosinate, Flavor, Xanthan Gum, Menthol, PEG-40 Hydrogenated Castor Oil, Zinc Citrate, Mentha Piperita (Peppermint) Oil, Mentha Viridis (Spearmint) Leaf Oil, Potassium Citrate, Siraitia Grosvenorii (Monkfruit) Fruit Extract, Sodium Saccharin, Potassium Bitartrate, Carbon Dioxide, Sodium Benzoate, Water, Maltodextrin, Carvone, Rebaudioside A, Alcohol Denat., Limonene, Sodium Chloride, Hydrolyzed Gardenia Florida Extract, Glycyrrhizic Acid, Gamma-Terpinene, Titanium Dioxide.

Questions?

+1 949-860-1860

PACKAGE LABEL

SmileSense

with BritePop Technology

Anticavity, Antigingivitis and Antisensitivity

Fluoride Toothpaste

3.8 oz / 108 g